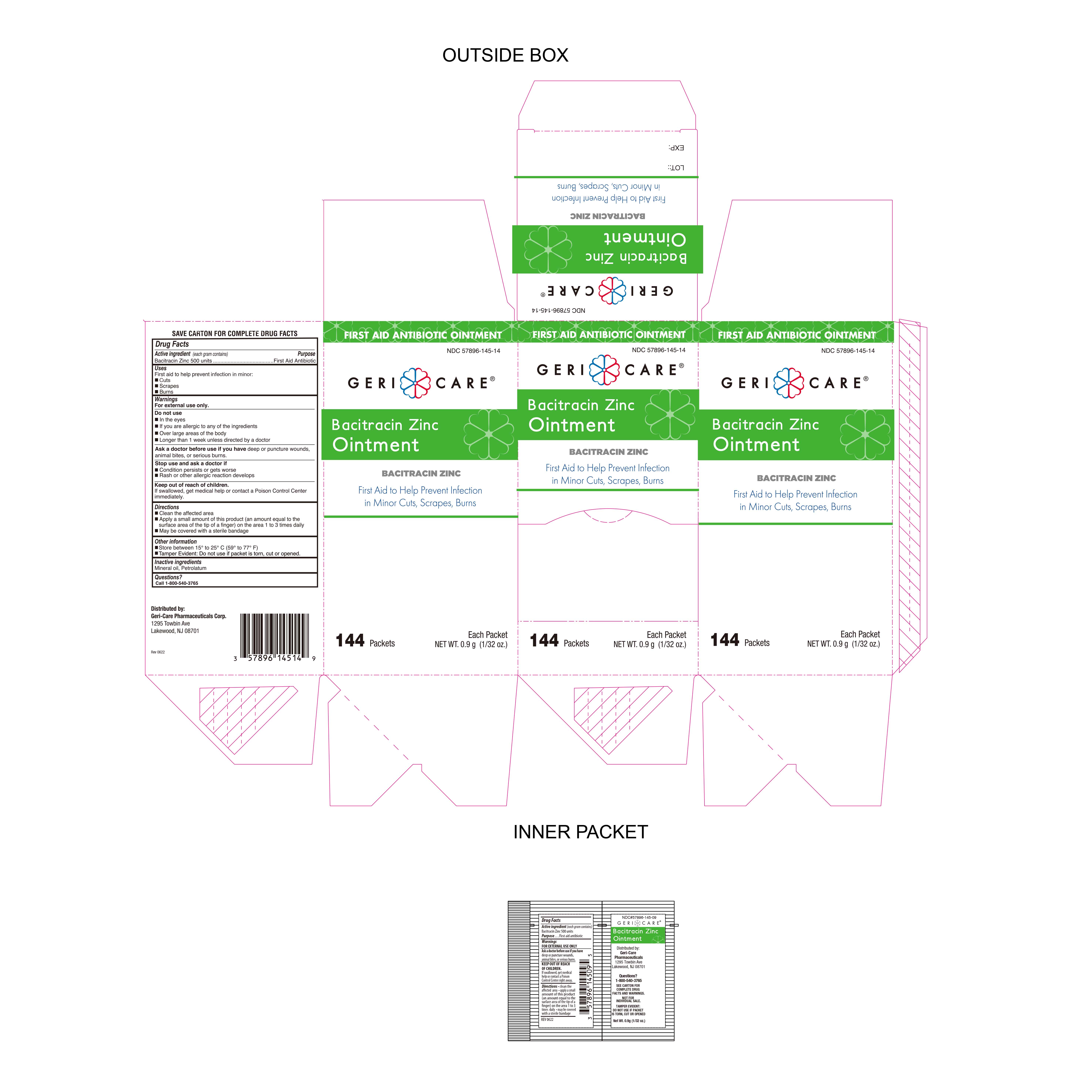 DRUG LABEL: Bacitracin Zinc
NDC: 57896-145 | Form: OINTMENT
Manufacturer: Geri-Care Pharmaceuticals, Corp.
Category: otc | Type: HUMAN OTC DRUG LABEL
Date: 20240102

ACTIVE INGREDIENTS: BACITRACIN ZINC 500 [USP'U]/1 g
INACTIVE INGREDIENTS: PETROLATUM; MINERAL OIL

Geri-Care Bacitracin Zinc Ointment

Active Ingredient

Bacitracin Zinc 500 Units

Purpose

First Aid Antibiotic

Uses

First Aid to help prevent infection in minor:

- cuts
- scrapes
- burns

Warnings

For External Use Only.

Do Not Use

- in eyes
- over large areas of the body
- if you are allergic to any of the ingredients
- Longer than 1 week unless directed by a doctor

Stop Use and Ask Doctor if

- Before use in case of deep puncture wounds, animal bites or serious burns
- The condition persists or gets worse
- A rash or allergic reaction develops

Directions

- Clean the affected area
- Apply a small amount of the product (an amount equal to the surface area of the tip of a finger) on the area 1 to 3 times daily
- May be covered with a sterile bandage

Keep out of reach of children

If swallowed, get medical help or contact a Poison Control Center Immediately.

Inactive Ingredients

Mineral oil, petrolatum

Questions

Call 1-800-540-3765

Storage Information

Store at room temperature 15° to 25°C (59° to 77°F).

Tamper Evident: Do not use if packet is torn, cut or opened.

Other Information

Distributed By:

GeriCare Pharmaceuticals Corp.

1295 Towbin Ave.

Lakewood, NJ 08701